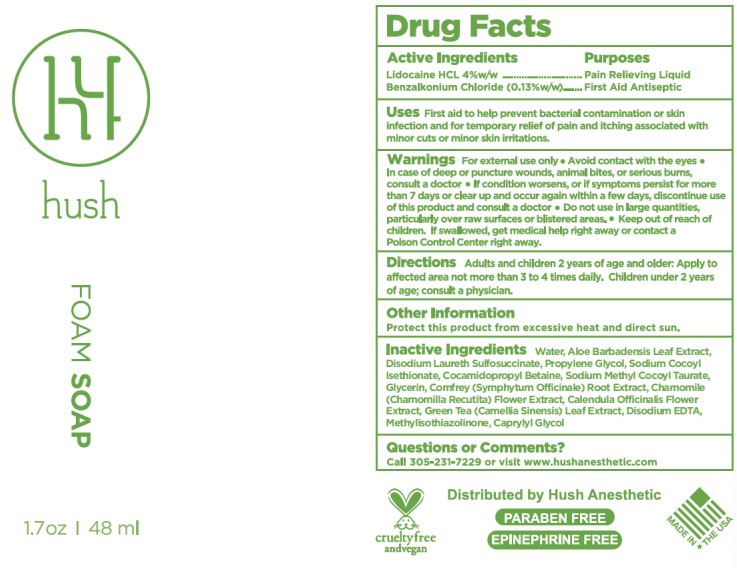 DRUG LABEL: Hush Anesthetic
NDC: 49947-003 | Form: SOAP
Manufacturer: HUSH Anesthetic
Category: otc | Type: HUMAN OTC DRUG LABEL
Date: 20220114

ACTIVE INGREDIENTS: LIDOCAINE 40 mg/1 g; BENZALKONIUM CHLORIDE 1.3 mg/1 g
INACTIVE INGREDIENTS: ALOE VERA LEAF; PEG-80 SORBITAN LAURATE; DISODIUM LAURETH SULFOSUCCINATE; MATRICARIA CHAMOMILLA FLOWERING TOP OIL; CALENDULA OFFICINALIS FLOWER; CAMELLIA SINENSIS WHOLE; SYMPHYTUM OFFICINALE WHOLE; COCAMIDOPROPYL BETAINE; PROPYLENE GLYCOL; CITRIC ACID ACETATE; CAPRYLYL GLYCOL; METHYLISOTHIAZOLINONE

HUSH Foam Soap

Active Ingredients

Lidocaine 4% w/w

Benzalkonium Chloride (0.13%) w/w

Purpose

Pain Relieving Liquid

First Aid Antiseptic

Uses

First aid to help prevent bacterial contamination or skin infection and for temporary relief of pain and itching associated with minor cuts or minor skin irritations.

Directions

Adults and children 2 years of age and older: Apply to affected area not more than 3 to 4 times daily. Children under 2 years of age, consult a physician.

Warnings

For external use only • Avoid contact with the eyes

Keep out of reach of children. If swallowed, get medical help right away or contact a Poison Control Center right away.

Do not use in large quantities, particularly over raw surfaces or blistered areas

STOP USE

In case of deep or puncture wounds, animal bites, or serious bites, consult a doctor • If condition worsens, or if symptoms persist for more than 7 days or clear up and occur again within a few days, discontinue use of this product and consult a doctor

Inactive ingredients

Aloe Barbadensis Leaf Extract, Aqua (Deionized Water), Calendula Officials Flower Extract, Caprylyl Glycol, Chamomile (Chamomilla Recutita) Flower Extract, Citric Acid, Cocamidopropyl Betaine, Comfrey (Symphytum Officinale) Root Extract, Disodium EDTA, Disodium Laureth Sulfosuccinate, Glycerin, Green Tea (Camellia Sinensis) Leaf Extract, Methylisothiazollnone, PEG-80 Sorbitan Laurate, Propylene Glycol

Other Information

Questions or Comments? Call 305-231-7229 or visit www.hushanesthetic.com